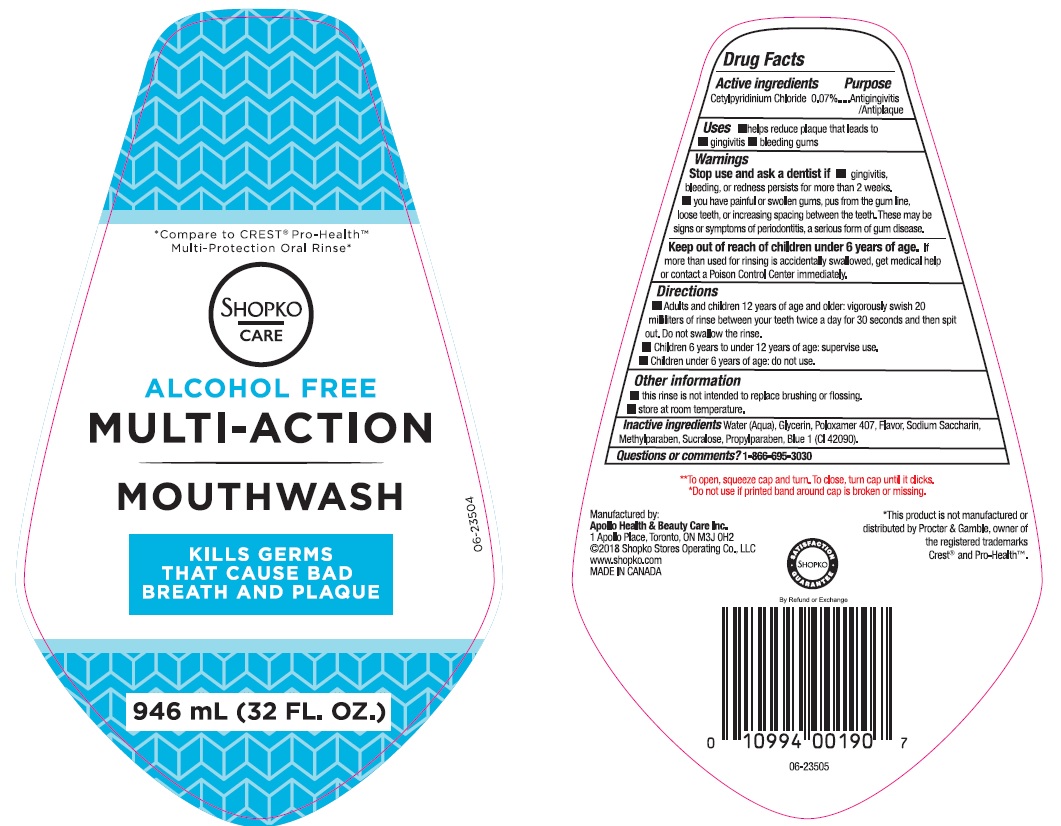 DRUG LABEL: Shopko Alcohol Free Multi Action
NDC: 63148-010 | Form: MOUTHWASH
Manufacturer: Apollo Health and Beauty Care Inc.
Category: otc | Type: HUMAN OTC DRUG LABEL
Date: 20180608

ACTIVE INGREDIENTS: CETYLPYRIDINIUM CHLORIDE 0.7 mg/1 mL
INACTIVE INGREDIENTS: WATER; GLYCERIN; POLOXAMER 407; SACCHARIN SODIUM; METHYLPARABEN; SUCRALOSE; PROPYLPARABEN; FD&C BLUE NO. 1

Drug Facts

Active ingredient

Cetylpyridinium Chloride 0.07%

Purpose

Antigingivitis/Antiplaque

Uses

- helps reduce plaque that lead to:
- gingivitis
- bleeding gums

Warnings

Stop use and ask a dentist if

- gingivitis, bleeding, or redness persists for more than 2 weeks
- you have painful or swollen gums, pus from the gum line, loose teeth, or increasing spacing between the teeth. These may be signs or symptoms of periodontitis, a serious form of gum disease.

Keep out of reach of children under 6 years of age.

If more than used for rinsing is accidentally swalowed, get medical help or contact a Poison Control Center immediately.

Directions

- Adults and children 12 years of age and older: vigorously swish 20 milliliters of rinse between your teeth twice a day for 30 seconds and then spit out. Do not swallow the rinse.
- Children 6 years to under 12 years of age: supervise use.
- Children under 6 years of age: do not use.

Other information

- this rinse is not intended to replace brushing or flossing.
- store at room temperature.

Inactive ingredients

Water (Aqua), Glycerin, Poloxamer 407, Flavor, Sodium Saccharin, Methylparaben, Sucralose, Propylparaben, Blue 1 (CI 42090).

Questions ro comments?

1-866-695-3030